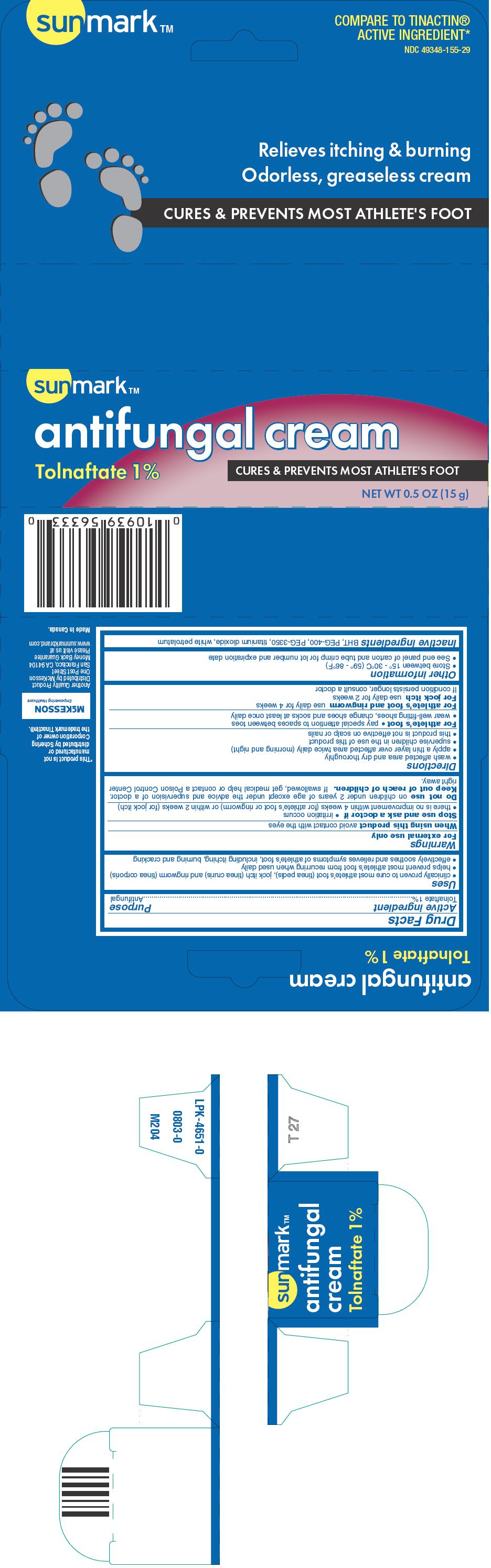 DRUG LABEL: sunmark
NDC: 49348-155 | Form: CREAM
Manufacturer: Strategic Sourcing Services LLC
Category: otc | Type: HUMAN OTC DRUG LABEL
Date: 20250707

ACTIVE INGREDIENTS: TOLNAFTATE 10 mg/1 g
INACTIVE INGREDIENTS: BUTYLATED HYDROXYTOLUENE; POLYETHYLENE GLYCOL 400; POLYETHYLENE GLYCOL 3350; TITANIUM DIOXIDE; PETROLATUM

sunmark™
antifungal

Drug Facts

Active ingredient

Tolnaftate 1%

Purpose

Antifungal

Uses

- clinically proven to cure most athlete's foot (tinea pedis), jock itch (tinea cruris) and ringworm (tinea corporis)
- helps prevent most athlete's foot from recurring when used daily
- effectively soothes and relieves symptoms of athlete's foot, including itching, burning and cracking

Warnings

For external use only

When using this productavoid contact with the eyes

Stop use and ask a doctor if

- irritation occurs
- there is no improvement within 4 weeks (for athlete's foot or ringworm) or within 2 weeks (for jock itch)

DO NOT USE

Do not useon children under 2 years of age except under the advice and supervision of a doctor.

Keep out of reach of children.If swallowed, get medical help or contact a Poison Control Center right away.

Directions

- wash affected area and dry thoroughly
- apply a thin layer over affected area twice daily (morning and night)
- supervise children in the use of this product
- this product is not effective on scalp or nails

For athlete's foot

- pay special attention to spaces between toes
- wear well-fitting shoes, change shoes and socks at least once daily

For athlete's foot and ringwormuse daily for 4 weeks

For jock itchuse daily for 2 weeks
If condition persists longer, consult a doctor

Other information

- Store between 15° - 30°C (59° - 86°F)
- See end panel of carton and tube crimp for lot number and expiration date

Inactive ingredients

BHT, PEG-400, PEG-3350, titanium dioxide, white petrolatum

Distributed by McKesson
One Post Street
San Francisco, CA 94104

PRINCIPAL DISPLAY PANEL - 15 g Tube Carton

sunmark™

antifungal cream

Tolnaftate 1%
CURES & PREVENTS MOST ATHLETE'S FOOT

NET WT 0.5 OZ (15 g)